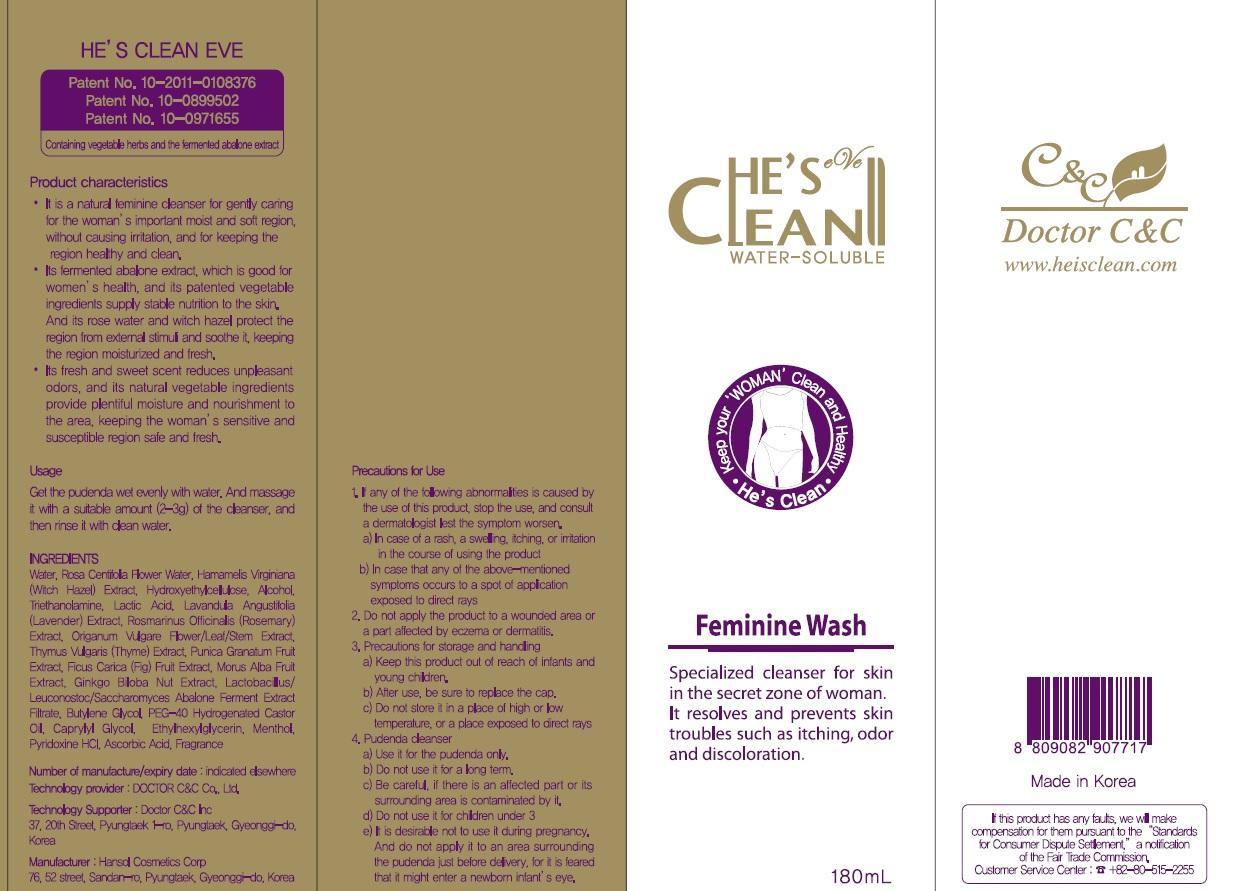 DRUG LABEL: HES CLEAN EVE
NDC: 42979-130 | Form: GEL
Manufacturer: DOCTOR C&C
Category: otc | Type: HUMAN OTC DRUG LABEL
Date: 20140514

ACTIVE INGREDIENTS: Alcohol 1.8 mg/180 mL
INACTIVE INGREDIENTS: Water; Witch Hazel

ACTIVE INGREDIENT

Active Ingredient: Alcohol 1%

INACTIVE INGREDIENT

Inactive ingredients:
Water, Rosa Centifolia Flower Water, Hamamelis Virginiana (Witch Hazel) Extract, Hydroxyethylcellulose, Triethanolamine, Lactic Acid, Lavandula Angustifolia (Lavender) Extract, Rosmarinus Officinalis (Rosemary) Extract, Origanum Vulgare Flower/Leaf/Stem Extract,
Thymus Vulgaris (Thyme) Extract, Punica Granatum Fruit Extract, Ficus Carica (Fig) Fruit Extract, Morus Alba Fruit Extract, Ginkgo Biloba Nut Extract, Lactobacillus/Leuconostoc/Saccharomyces Abalone Ferment Extract Filtrate, Butylene Glycol, PEG-40 Hydrogenated Castor Oil, Caprylyl Glycol, Ethylhexylglycerin, Menthol, Pyridoxine HCl, Ascorbic Acid, Fragrance

PURPOSE

Purpose: Antifungal

Precautions for use

1. If any of the following abnormalities is caused by the use of this product, stop the use, and consult a dermatologist lest the symptom worsen.
a) In case of a rash, a swelling, itching, or irritation in the course of using the product.
b) In case that any of the above mentioned symptoms occurs to a spot of application exposed to direct rays.
2. Do not apply the product to a wounded area or a part affected by eczema or dermatitis.
3. Precautions for storage and handling
a) Keep this product out of reach of infants and young children.
b) After use, be sure to replace the cap.
c) Do not store it in a place of high or low temperature, or a place exposed to direct rays.
4. Pudenda cleanser
a) Use it for the pudenda only.
b) Do not use it for a long term.
c) Be careful, if there is an affected part or its surrounding area is contaminated by it.
d) Do not use it for children under 3.
e) It is desirable not to use it during pregnancy. And do not apply it to an area surrounding the pudenda just before delivery.

KEEP OUT OF REACH OF CHILDREN

Keep this product out of reach of infants and young children.

Usage

Get the pudenda wet evenly with water. And massage it with a suitable amount (2-3g) of the cleanser, and then rinse it with clean water.

Usage

Get the pudenda wet evenly with water. And massage it with a suitable amount (2-3g) of the cleanser, and then rinse it with clean water.